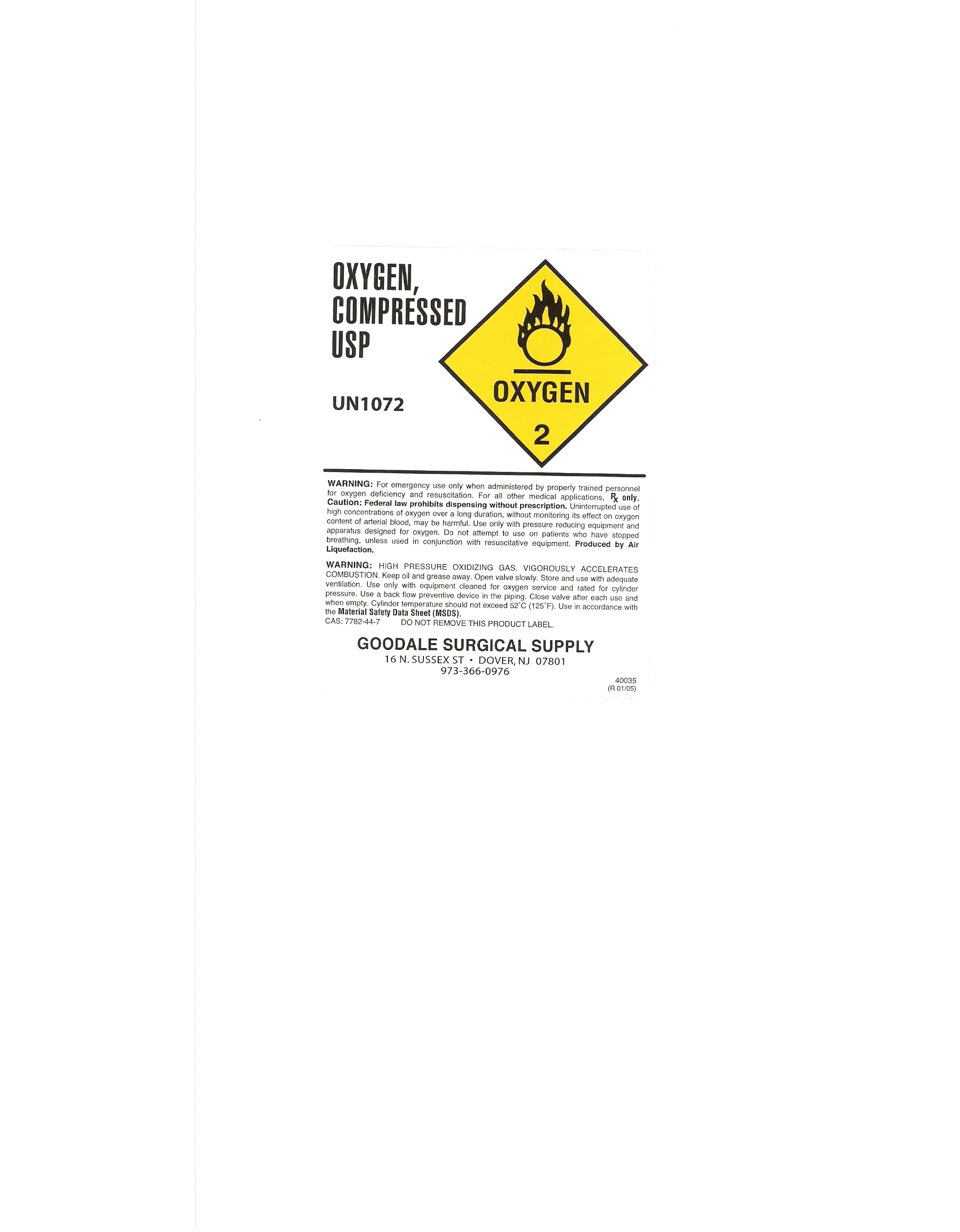 DRUG LABEL: Oxygen
NDC: 50597-010 | Form: GAS
Manufacturer: W. H. Goodale Co. Inc.
Category: prescription | Type: HUMAN PRESCRIPTION DRUG LABEL
Date: 20110811

ACTIVE INGREDIENTS: OXYGEN 210 mL/1 L

PACKAGE LABEL

Enter section text here